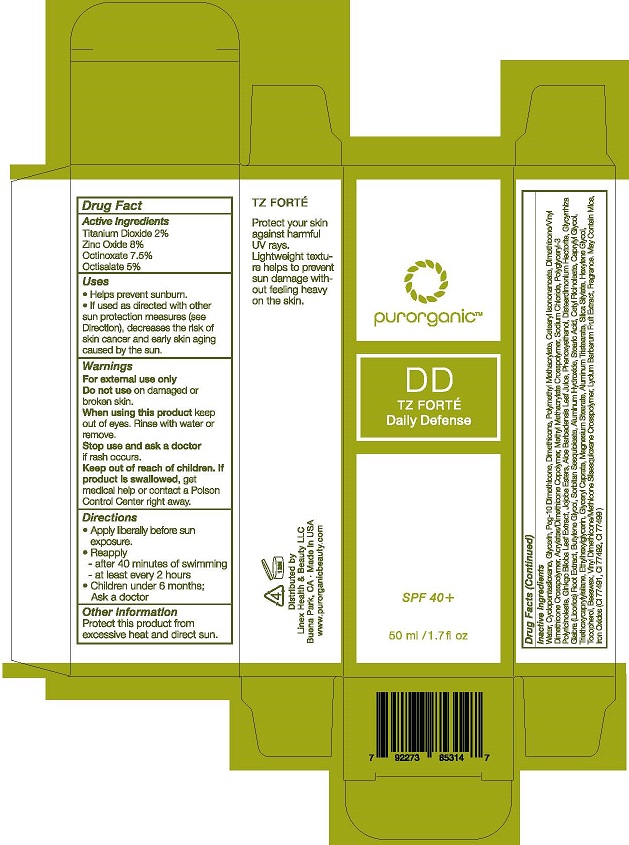 DRUG LABEL: DD TZ FORTE
NDC: 69769-102 | Form: LOTION
Manufacturer: LINEX HEALTH & BEAUTY
Category: otc | Type: HUMAN OTC DRUG LABEL
Date: 20221229

ACTIVE INGREDIENTS: TITANIUM DIOXIDE 2 g/100 mL; ZINC OXIDE 8 g/100 mL; OCTINOXATE 7.5 g/100 mL; OCTISALATE 5 g/100 mL
INACTIVE INGREDIENTS: WATER; CYCLOMETHICONE 5; GLYCERIN; PEG-10 DIMETHICONE (600 CST); DIMETHICONE 100; POLY(METHYL METHACRYLATE; 450000 MW); DIMETHICONE/VINYL DIMETHICONE CROSSPOLYMER (SOFT PARTICLE); DIMETHICONE CROSSPOLYMER (450000 MPA.S AT 12% IN CYCLOPENTASILOXANE); METHYL METHACRYLATE; SODIUM CHLORIDE; POLYGLYCERIN-3; GINKGO BILOBA WHOLE; MICA; CETEARYL ISONONANOATE; ALOE VERA LEAF; PHENOXYETHANOL; DISTEARDIMONIUM HECTORITE; LICORICE; BUTYLENE GLYCOL; SORBITAN SESQUIOLEATE; ALUMINUM HYDROXIDE; STEARIC ACID; CETYL RICINOLEATE; CAPRYLYL GLYCOL; TRIETHOXYCAPRYLYLSILANE; ETHYLHEXYLGLYCERIN; GLYCERYL CAPRATE; MAGNESIUM STEARATE; ALUMINUM STEARATES; SILICA DIMETHYL SILYLATE; HEXYLENE GLYCOL; TOCOPHEROL; YELLOW WAX; JOJOBA OIL, RANDOMIZED; POLYMETHYLSILSESQUIOXANE (11 MICRONS); LYCIUM BARBARUM FRUIT; FERRIC OXIDE RED; FERRIC OXIDE YELLOW; FERROSOFERRIC OXIDE

Linex (as PLD) - TZ FORTE (69769-102)

ACTIVE INGREDIENTS

TITANIUM DIOXIDE 2%

ZINC OXIDE 8%

OCTINOXATE 7.5%

OCTISALATE 5%

PURPOSE

SUNSCREEN

USES

- HELPS PREVENT SUNBURN.
- IF USED AS DIRECTED WITH OTHER SUN PROTECTION MEASURES (SEE DIRECTION), DECREASES THE RISK OF SKIN CANCER AND EARLY SKIN AGING CAUSED BY THE SUN.

WARNINGS

FOR EXTERNAL USE ONLY.

DO NOT USE ON DAMAGED OR BROKEN SKIN.

WHEN USING THIS PRODUCT KEEP OUT OF EYES. RINSE WITH WATER TO REMOVE.

STOP USE AND ASK A DOCTOR IF RASH OCCURS.

KEEP OUT OF REACH OF CHILDREN. IF PRODUCT IS SWALLOWED, GET MEDICAL HELP OR CONTACT A POISON CONTROL CENTER RIGHT AWAY.

DIRECTIONS

- APPLY LIBERALLY BEFORE SUN EXPOSURE.
- REAPPLY -
- AFTER 40 MINUTES OF SWIMMING
- AT LEAST EVERY 2 HOURS
- CHILDREN UNDER 6 MONTHS; ASK A DOCTOR.

OTHER INFORMATION

PROTECT THIS PRODUCT FROM EXCESSIVE HEAT AND DIRECT SUN.

INACTIVE INGREDIENTS

WATER, CYCLOPENTASILOXANE, GLYCERIN, PEG-10 DIMETHICONE, DIMETHICONE, POLYMETHYL METHACRYLATE, CETEARYL ISONONANOATE, DIMETHICONE/VINYL DIMETHICONE CROSSPOLYMER, ACRYLATES/DIMETHICONE COPOLYMER, METHYL METHACRYLATE CROSSPOLYMER, SODIUM CHLORIDE, POLYGLYCERYL-3 POLYRICINOLEATE, GINKGO BILOBA LEAF EXTRACT, JOJOBA ESTERS, ALOE BARBADENSIS LEAF JUICE, PHENOXYETHANOL, DISTEARDIMONIUM HECTORITE, GLYCYRRHIZA GLABRA (LICORICE) ROOT EXTRACT, BUTYLENE GLYCOL, SORBITAN SESQUIOLEATE, ALUMINUM HYDROXIDE, STEARIC ACID, CETYL RICINOLEATE, CAPRYLYL GLYCOL, TRIETHOXYCAPRYLYLSILANE, ETHYLHEXYLGLYCERIN, GLYCERYL CAPRATE, MAGNESIUM STEARATE, ALUMINUM TRISTEARATE, SILICA SILYLATE, HEXYLENE GLYCOL, TOCOPHEROL, BEESWAX, VINYL DIMETHICONE/METHICONE SESQUIOXANE CROSSPOLYMER, LYCIUM BARBARUM FRUIT EXTRACT, FRAGRANCE. MAY CONTAIN: MICA, IRON OXIDES (CI 77491, CI 77492, CI 77499)